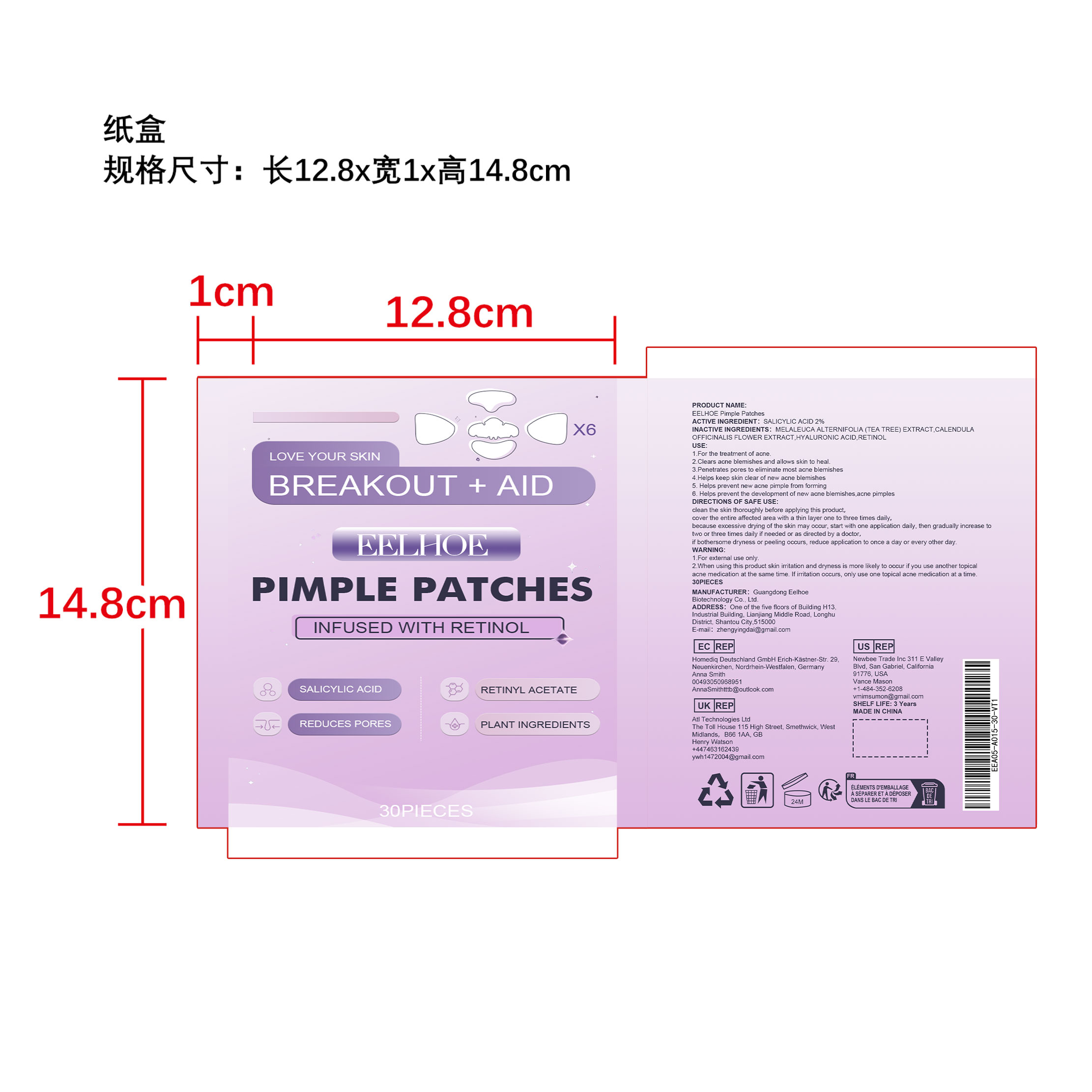 DRUG LABEL: EELHOE Pimple Patches
NDC: 84832-001 | Form: PATCH
Manufacturer: Guangdong Eelhoe Biotechnology Co., Ltd.
Category: otc | Type: HUMAN OTC DRUG LABEL
Date: 20240925

ACTIVE INGREDIENTS: SALICYLIC ACID 2 g/100 g
INACTIVE INGREDIENTS: HYALURONIC ACID; CALENDULA OFFICINALIS FLOWER; TEA TREE OIL; RETINOL

ACTIVE INGREDIENT

SALICYLIC ACID 2%

INACTIVE INGREDIENTS

MELALEUCA ALTERNIFOLIA (TEA TREE) EXTRACT.CALENDULA
OFFICINALIS FLOWER EXTRACT HYALURONIC ACID.RETINOL

USE

1.For the treatment of acne.
2.Clears acne blemishes and allows skin to heal

3.Penetrates pores to eliminate most acne blemishes

4.Helps keep skin clear of new acne blemishes

5.Helps prevent new acne pimple from forming6.Helps prevent the development of new acne blemishes,acne pimples

Direction

clean the skin thoroughly before applying this product,
cover the entire affected area with a thin layer one to three times daily,because excessive drying of the skin may occur, start with one application daily, then gradually increase totwo or three times daily if needed or as directed by a doctor,if bothersome dryness or peeling occurs, reduce application to once a day or every other day.

Warning

1.For external use only.
2.When using this product skin irritation and dryness is more likely to occur if you use another topicalacne medication at the same time, lf irritation occurs, only use one topical acne medication at a time

DOSAGE AND ADMINISTRATION

none

KEEP OUT OF REACH OF CHILDREN

none

PURPOSE

none